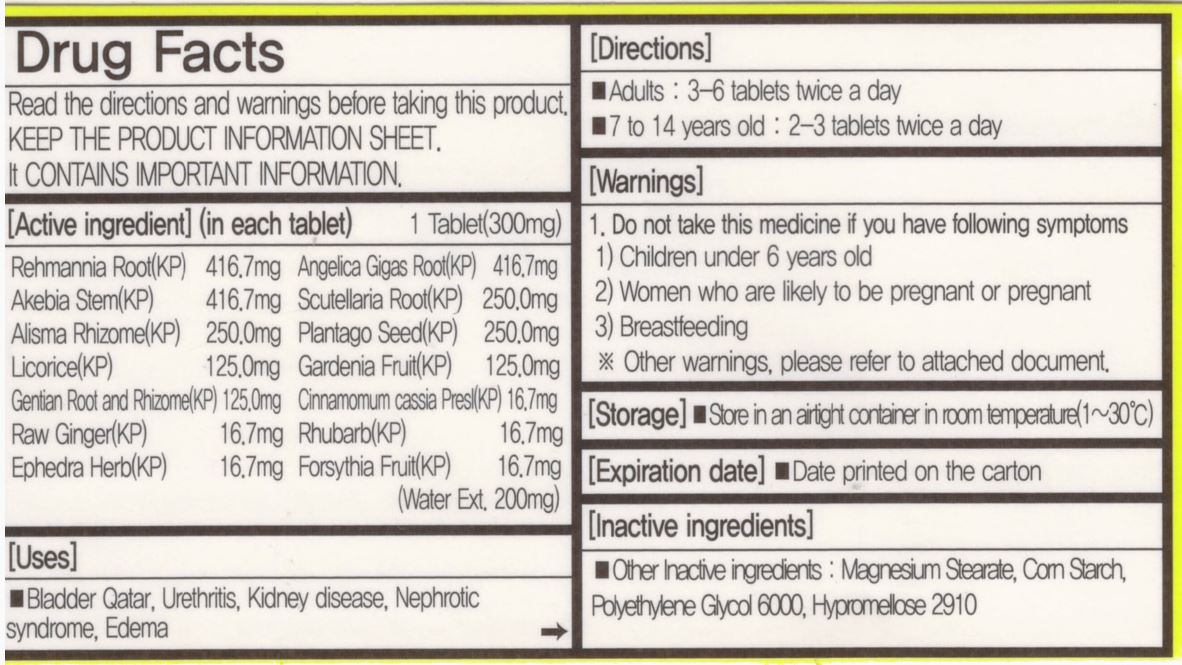 DRUG LABEL: YOBISIN
NDC: 72988-0012 | Form: TABLET
Manufacturer: Lydia Co., Ltd.
Category: otc | Type: HUMAN OTC DRUG LABEL
Date: 20231216

ACTIVE INGREDIENTS: RHUBARB 16.7 mg/1 1; REHMANNIA GLUTINOSA ROOT 416.7 mg/1 1; ANGELICA GIGAS ROOT 416.7 mg/1 1; AKEBIA STEM 416.7 mg/1 1; SCUTELLARIA BAICALENSIS ROOT 250 mg/1 1; LICORICE 125 mg/1 1; ALISMA PLANTAGO-AQUATICA ROOT 250 mg/1 1; FORSYTHIA SUSPENSA FRUIT 16.7 mg/1 1; PLANTAGO SEED 250 mg/1 1; GINGER 16.7 mg/1 1; CHINESE CINNAMON 16.7 mg/1 1
INACTIVE INGREDIENTS: MAGNESIUM STEARATE

Drug Facts

ACTIVE INGREDIENT

rehmannia root, angelica gigas root, akebia stem, scutellaria root, alisma rhizome, plantago seed, licorice, gardenia fruit, gentian root and rhizome, cinnamomum cassia presl, raw ginger, rhubarb, ephdra heab, forsythia fruit

INACTIVE INGREDIENT

magnesium stearate, corn starch, polyethylene glycol 6000, hypromellose 2910

PURPOSE

bladder qatar, urethritis, kidney disease, nephrotic syndrome, edema

keep out of reach of the children

INDICATIONS AND USAGE

adults: 3~6 tablets twice a day

7 to 14 years old: 2-3 tablets twice a day

WARNINGS

do not take this medicine if you have following symptoms

children under 6 years old

women who are likely to be pregnant or pregnant

breastfeeding

DOSAGE AND ADMINISTRATION

for oral use only